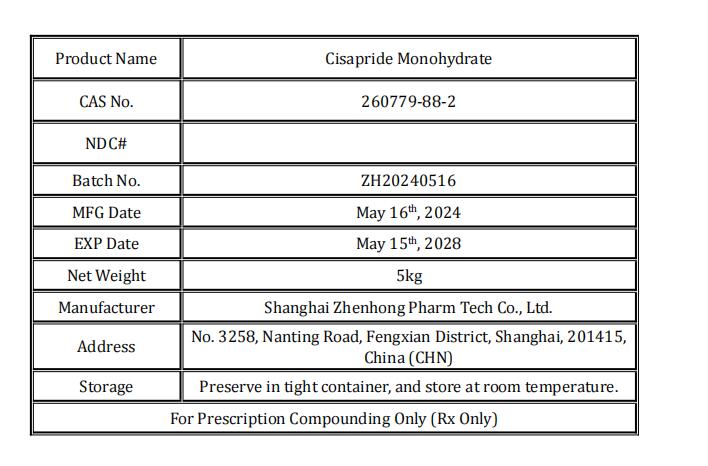 DRUG LABEL: Cisapride Monohydrate
NDC: 86228-116 | Form: POWDER
Manufacturer: Shanghai Zhenhong Pharm Tech Co., Ltd.
Category: other | Type: BULK INGREDIENT - ANIMAL DRUG
Date: 20250916

ACTIVE INGREDIENTS: Cisapride Monohydrate 1 kg/1 kg

Cisapride Monohydrate